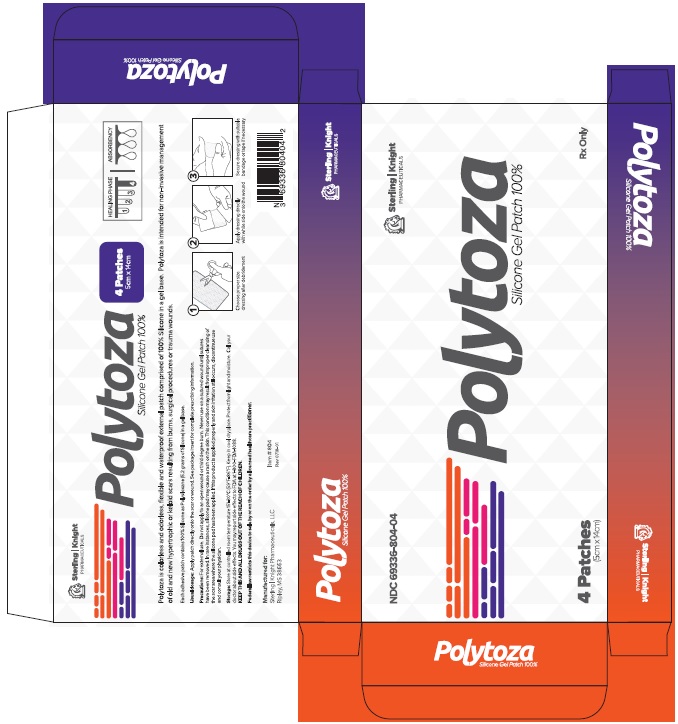 DRUG LABEL: Polytoza
NDC: 69336-804
Manufacturer: Sterling-Knight Pharmaceuticals, LLC
Category: other | Type: MEDICAL DEVICE
Date: 20200212

Polytoza
Silicone Gel Patch 100%
Rx Only (Prescription Only)

DESCRIPTION

Polytoza is colorless and odorless, flexible and waterproof external patch comprised of 100% Silicone in a gel base. Polytoza is intended for non-invasive management of old and new hypertrophic or keloid scars resulting from burns, surgical procedures or trauma wounds.

Clinical Pharmacology

The exact mechanism of silicone gel patches in improving the appearance of scar tissue remains unknown. However, numerous mechanisms have been suggested to explain the efficacy of silicone gel patch, including hydration, pressure, temperature, oxygen transmission and silicone absorption. There is some evidence that the treatment affects the stratum corneum and, by reducing evaporation, restores better homeostasis in the tissue. In keloid and hypertrophic scarring, the stratum corneum allows more evaporation of water from the underlying tissue than occurs in normal skin. Silicone patches may prevent this, keeping the stratum corneum in optimal hydration and protecting the skin from environmental hazards, both of which can reduce abnormal scarring. The silicone gel patch may also affect the stratum corneum by inhibiting mast cell activity, diminishing edema, vasodilatation and excessive extracellular matrix formation but the simple changes in temperature, pressure, oxygen tension and hydration produced by wound coverage probably constitute the main mechanism of action. Another hypothesis is that the effect of static electricity on silicone may influence the alignment of collagen deposition.

Indication and Uses

For external use only. Polytoza is intended for non-invasive management of old and new hypertrophic or keloid scars resulting from burns, surgical procedures or trauma wounds. It is effective for the management of both existing and new hypertrophic or keloid scars and as a prophylactic treatment on closed wounds.

Contraindications

Polytoza is contraindicated in patients with known hypersensitivity to silicone or any of the listed ingredients.

Warnings

For external use. Do not apply to an open wound or third degree burn. Never use on a sutured wound until sutures have been removed. In rare instances, silicone patch may cause a rash on the skin. This condition may result from improper cleansing of the scar area where the silicone patch has been applied. If this product is applied properly and skin irritation still occurs, discontinue use and consult your physician.

Ingredients

Each Polytoza patch contains: 100% Silicone as Polysiloxane (5.2 grams of Silicone) in a gel base.

Precautions

Stop use and ask a doctor if irritation develops. In rare instances, silicone sheets may cause a rash on the skin. This condition may result from improper cleansing of the scar area where the silicone patch has been applied. If this product is applied properly and skin irritation still occurs, discontinue use and consult your physician. If ingested, get medical help or contact Poison Control Center right away. KEEP THIS AND ALL MEDICATION OUT OF THE REACH OF CHILDREN.

Call your doctor about side effects. You may report side effects to FDA at 1-800-FDA-1088. KEEP THIS AND ALL DRUGS OUT OF THE REACH OF CHILDREN.

Caution:

Federal law restricts this device to sale by or on the order by a licensed healthcare practitioner.

Adverse Reactions

Polytoza may cause transient redness stinging, burning or irritation, however, it normally disappears when discontinuing the use of the patches.

Dosage and Administration

1. Wash your hands and the scar area with soap and water. Dry thoroughly.
2. Cut the patch to fit the scar area so that the edges of the gel patch extend at least 1/4'' beyond the scar on all sides.
3. Peel of the strip and place the sticky side of the patch directly onto the scar or wound. Leave on for 8-12 hours per day then remove. Do not discard the mylar release strip.
4. When not wearing the patch, place the patch back onto the mylar release strip.
5. Discard the patch and replace with a new patch every 5 - 7 days.

How Supplied

Polytoza is supplied in:
Cartons containing 4 Patches packed in individual envelopes containing 1 patch each (5cmx14cm),
NDC 69336-804-04

Storage:

Storage: Store at controlled room temperature 15°-30°C (59°F-86°F). Keep in cool dry place. Protect from light and moisture.

Distributed By:
Sterling-Knight Pharmaceuticals, LLC
Ripley, MS 38663
Rev 0718-1
Product Code: 804

PRINCIPAL DISPLAY PANEL

Sterling-Knight Pharmaceuticals, LLC
Ripley, MS 38663
Rev 0718-1

Product Code: 804

Polytoza
Silicone Gel Patch 100%

Rx Only (Prescription Only)